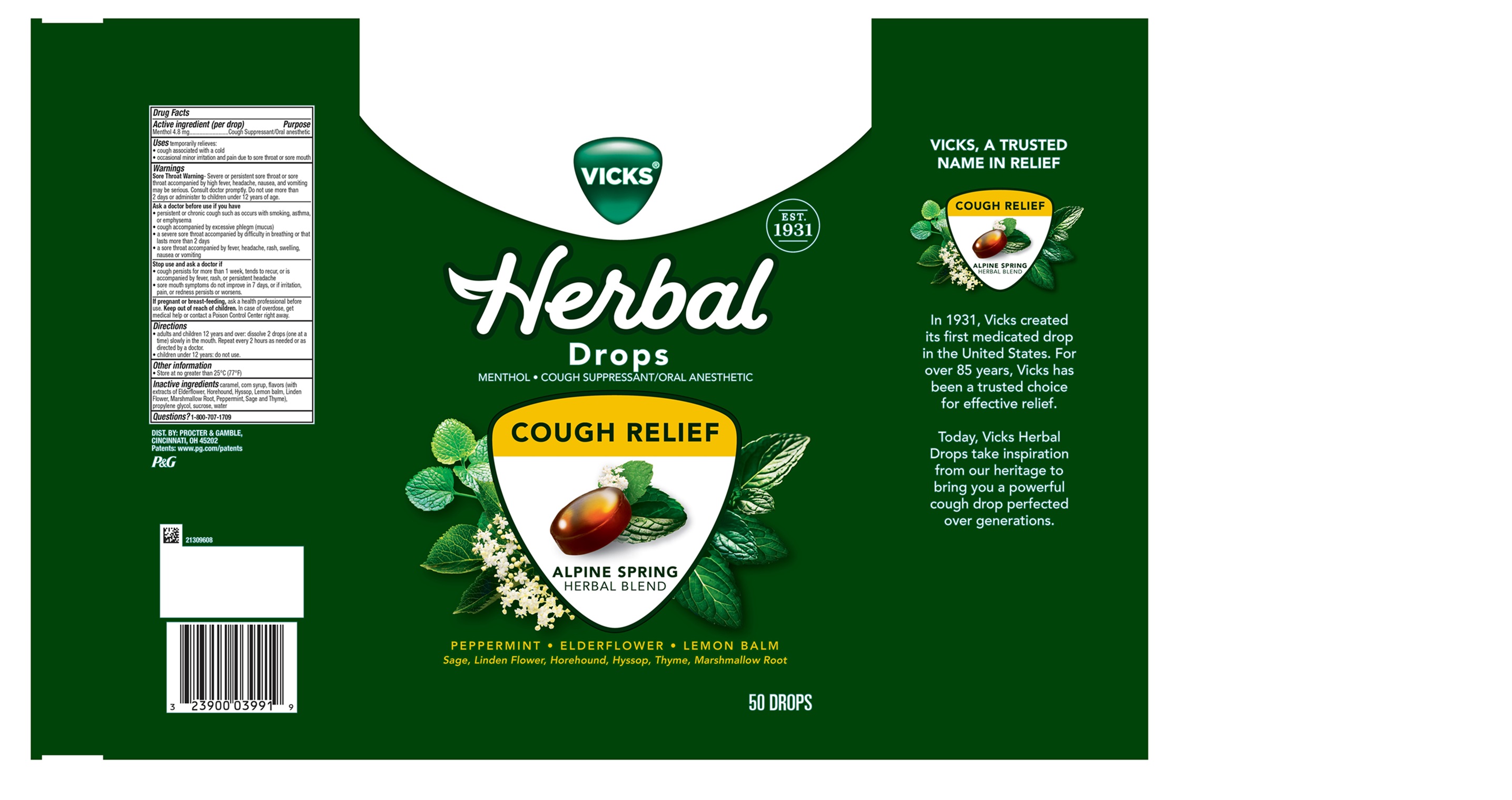 DRUG LABEL: Vicks Herbal Drops
NDC: 84126-323 | Form: LOZENGE
Manufacturer: The Procter & Gamble Manufacturing Company
Category: otc | Type: HUMAN OTC DRUG LABEL
Date: 20250701

ACTIVE INGREDIENTS: MENTHOL 4.8 mg/1 1
INACTIVE INGREDIENTS: SUCROSE; CORN SYRUP; CARAMEL; PROPYLENE GLYCOL; WATER

Vicks® Herbal Drops

Drug Facts

Active ingredient (per drop)

Menthol 4.8 mg

Purpose

Cough Suppresesant/Oral anesthetic

Uses

temporarily relieves

- cough associated with a cold
- occassional minor irritation and pain due to sore throat or sore mouth

Warnings

Sore Throat Warning-

Severe or persistent sore throat or sore throat accompanied by high fever, headache, nausea, and vomiting may be serious. Consult doctor promptly. Do not use more than 2 days or administer to children under 12 years of age.

Ask a doctor before use if you have

- persistent or chronic cough such as occurs with smoking, asthma, or emphysema
- cough accompanied by excessive phlegm (mucus)
- a severe sore throat accompanied by difficulty in breathing or that lasts more than 2 days
- a sore throat accompanied by fever, headache, rash, swelling, nausea or vomiting

Stop use and ask a doctor if

- cough persists more than 1 week, tends to rcur, or is accompaned by fever, rash, or persistent headache
- sore mouth symptoms do not improve in 7 days, or if irritation, pain, or redness persists or worsens.

If pregnant or breast-feeding,

ask a health professional before use.

Keep out of reach of children.

OVERDOSAGE

In case of overdose, get medical help or contact a Poison Control Center right away

Directions

- adults and children 12 years and over: dissolve 2 drops (one at a time) slowly in the mouth. Repeat every 2 hours as needed or as directed by a doctor.
- children 12 years and under: do not use

Other information

- Store at no greater than 25°C (77°F)

Inactive ingredients

caramel, corn syrup, flavors (with extracts of Elderflower, Horehound, Hyssop, Lemon balm, Linden Flower, Marshmallow Root, Peppermint, Sage and Thyme), propylene glycol, sucrose, water

Questions?

1-800-707-1709

DIST. BY:

PROCTER & GAMBLE

CINCINNATI, OH 45202

PACKAGE LABEL

VICKS®

Herbal Drops

MENTHOL • COUGH SUPPRESSANT/ORAL ANESTHETIC

COUGH RELIEF

ALPINE SPRING

HERBAL BLEND

PEPPERMINT • ELDERFLOWER • LEMON BALM

Sage, Linden Flower, Horehound, Hyssop, Thyme, Marshmallow Root

50 DROPS